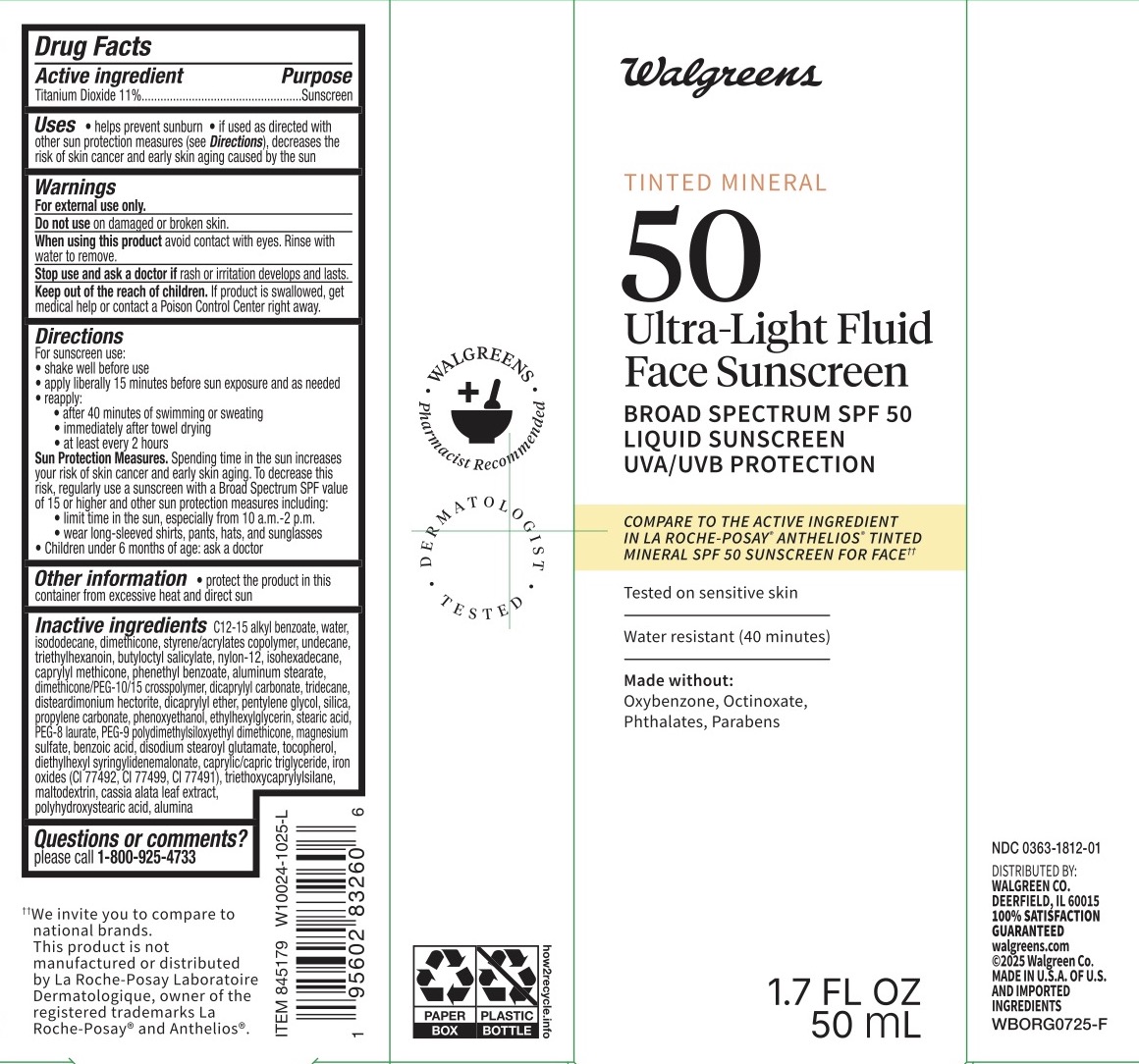 DRUG LABEL: Walgreens SPF 50 Tinted Mineral Fluid
NDC: 0363-1812 | Form: LOTION
Manufacturer: Walgreens
Category: otc | Type: HUMAN OTC DRUG LABEL
Date: 20251109

ACTIVE INGREDIENTS: TITANIUM DIOXIDE 11 g/100 mL
INACTIVE INGREDIENTS: MAGNESIUM SULFATE; POLYHYDROXYSTEARIC ACID (2300 MW); PEG-9 POLYDIMETHYLSILOXYETHYL DIMETHICONE; PHENOXYETHANOL; DISTEARDIMONIUM HECTORITE; PROPYLENE CARBONATE; ISOHEXADECANE; PHENETHYL BENZOATE; PEG-8 LAURATE; BENZOIC ACID; CI 77499; UNDECANE; TRIETHOXYCAPRYLYLSILANE; SENNA ALATA LEAF; ALUMINA; ISODODECANE; STYRENE/ACRYLAMIDE COPOLYMER (MW 500000); TRIETHYLHEXANOIN; DIMETHICONE 200; MALTODEXTRIN; CI 77491; DISODIUM STEAROYL GLUTAMATE; TRIDECANE; DICAPRYLYL ETHER; TOCOPHEROL; DIETHYLHEXYL SYRINGYLIDENEMALONATE; WATER; BUTYLOCTYL SALICYLATE; CAPRYLIC/CAPRIC TRIGLYCERIDE; CI 77492; ALUMINUM STEARATE; PENTYLENE GLYCOL; C12-15 ALKYL BENZOATE; NYLON-12; DIMETHICONE/PEG-10/15 CROSSPOLYMER; DICAPRYLYL CARBONATE; CAPRYLYL METHICONE; SILICON DIOXIDE; ETHYLHEXYLGLYCERIN; STEARIC ACID

ACTIVE INGREDIENT

Titanium Dioxide 11%

PURPOSE

Sunscreen

INDICATIONS AND USAGE

Helps prevent sunburn. If used as directed with other sun protection measures (see Directions), decreases the risk of skin cancer and early skin aging caused by the sun.

WARNINGS

For external use only.

do not use on damaged or broken skin.

When using this product avoid contact with eyes. Rinse with water to remove.

Stop use and ask a doctor if rash or irritation developss and lasts.

KEEP OUT OF REACH OF CHILDREN

If product is swallowed, get medical help or contact a Poison Control Center right away.

DOSAGE AND ADMINISTRATION

For sunscreen use: shake well before use, apply liberally 15 minutes before sun exposure and as needed, reapply:

after 40 minutes of swimming or sweating, immediately after towel drying, and at least every 2 hours.

Sun Protection Measures. Spending time in the sun increases your risk of skin cancer and early skin aging. To decrease this risk, regularly use a sunscreen with a Broad Spectrum SPF value of 15 or higher and other sun protection measures including:

limit time in the sun, especially from 10 a.m. - 2 p.m., wear long-sleeved shirts, pants, hats, and sunglasses.

Children under 6 months of age: ask a doctor.

INACTIVE INGREDIENT

C12-15 alkyl bonzoate, water, isododecane, diemthicone, styrene/acrylates copolymer, undecane, triethylhexanoin, butyloctyl salicylate, nylon-12, isohexadecane, caprylyl methicone, phenethyl benzoate, aluminum stearate, dimethicone/PEG-10/15 crosspolymer, dicaprylyl carbonate, tridecane, disteardimonium hectorite, dicaprylyl ether, pentyle glycol, silica, propylene carbonate, phenoxyethanol, ethylhexylglycerin, stearic acid, PEG-8 laurate, PEG-9 polydimethylsiloxyethyl dimethicone, magnesium sulfate, benzoic acid, disodium stearoyl glutamate, tocopherol, diethylhexyl syringylidenemalonate, caprylic/capric triglyceride, iron oxides (CI 77492, CI 77499, CI 77491), triethoxycaprylysilane, maltodextrin, cassia alata leaf extract, polyhydroxystearic acid, alumina